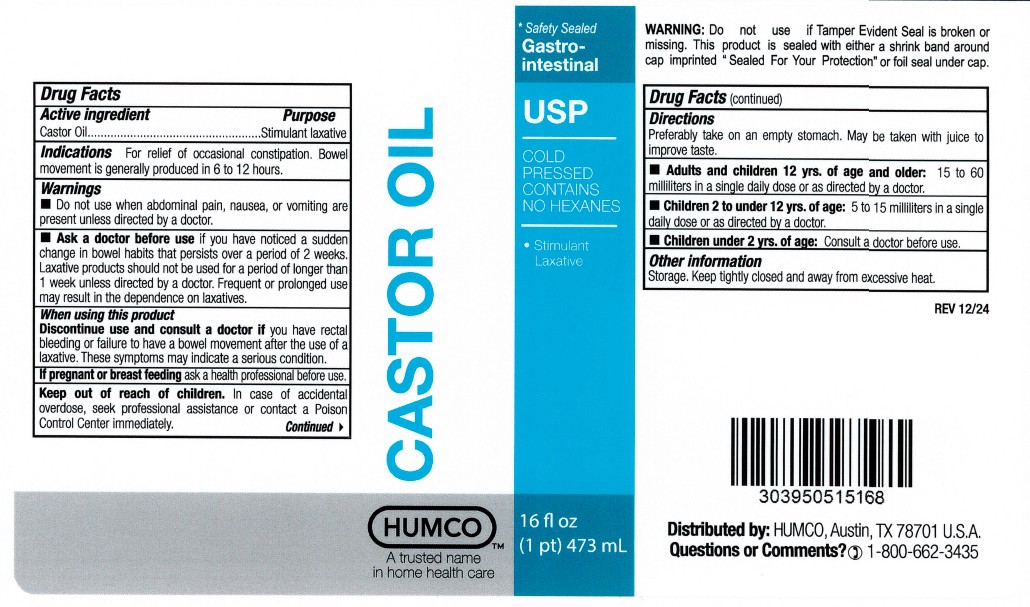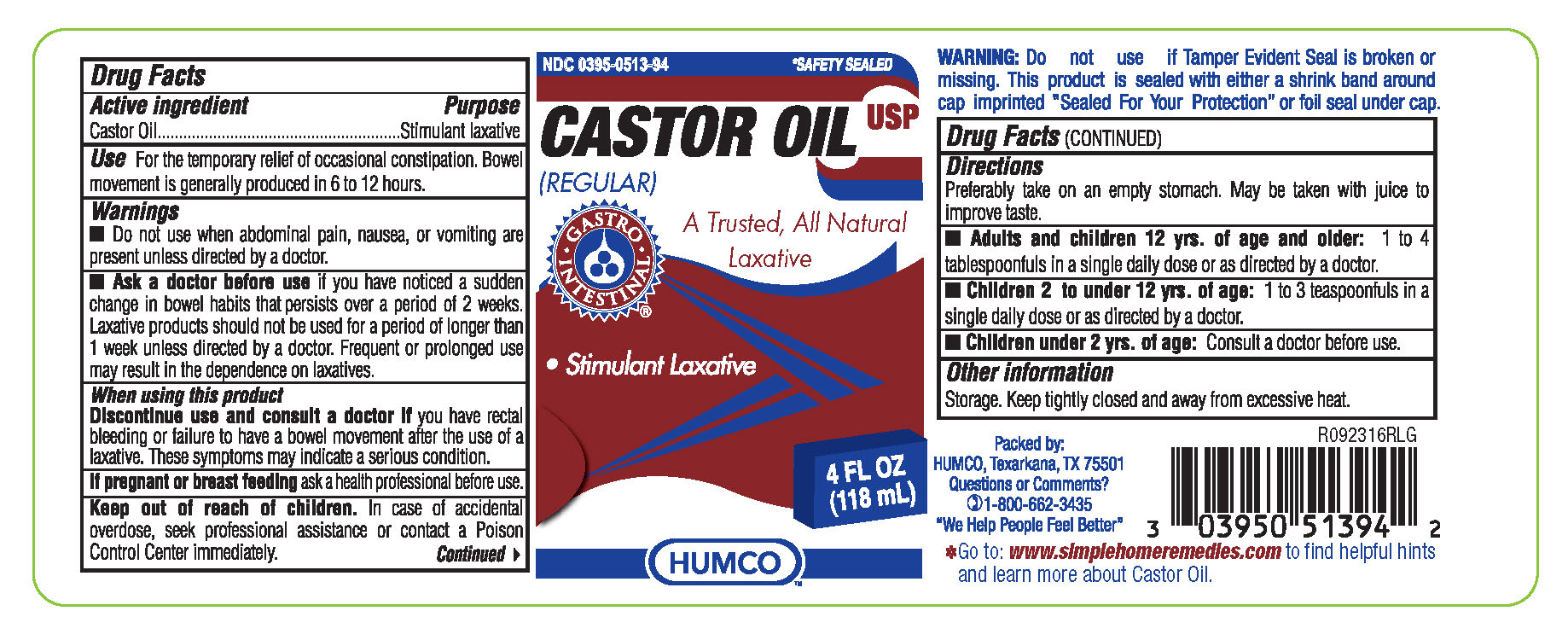 DRUG LABEL: Humco Castor Oil (Regular)
NDC: 0395-0513 | Form: LIQUID
Manufacturer: Humco Holding Group, Inc.
Category: otc | Type: HUMAN OTC DRUG LABEL
Date: 20251218

ACTIVE INGREDIENTS: CASTOR OIL 1 mg/1 mL
INACTIVE INGREDIENTS: WATER

Humco Castor Oil, USP (Regular)

Active Ingredient

Castor Oil

Purpose

Stimulant laxative

Uses

For the temporary relief of ocassional constipation. Bowel movement is generally produced in 6 to 12 hours.

Warnings

Do not use when abdominal pain, nausea, or vomiting are present unless directed by a doctor.

Ask a doctor before use.

If you have noticed a sudden change in bowel habits that persists over a period of two weeks. Laxative products should not be used for a period of longer than 1 week unless directed by a doctor. Frequent or prolonged use may result in dependence on laxatives.

When using this product:

Discontinue use and consult a doctor if you have rectal bleeding or failure to have a bowel movement after the use of a laxative. These symptoms may indicate a serious condition.

If pregnant or breastfeeding ask a health professional before use.

Keep out of reach of children

In case of accidental overdose, seek professional assistance or contact a Poison Control Center immediately.

Directions

- Adults and children 12 yrs. of age and older: 15 to 60 milliliters in a single day or as directed by a doctor.
- Children 2 to under 12 years of age: 5 to 15 milliliters in a single daily dose or as directed by a doctor.
- Children under 2 yrs. of age: Consult a doctor before use.

RECENT MAJOR CHANGES

Adults and children 12 yrs. of age and older: 15 to 60 milliliters in a single daily dose or as directed by a doctor.

Children 2 to under 12 yrs. of age: 5 to 15 milliliters in a single daily dose or as directed by a doctor.

Inactive Ingredient

None